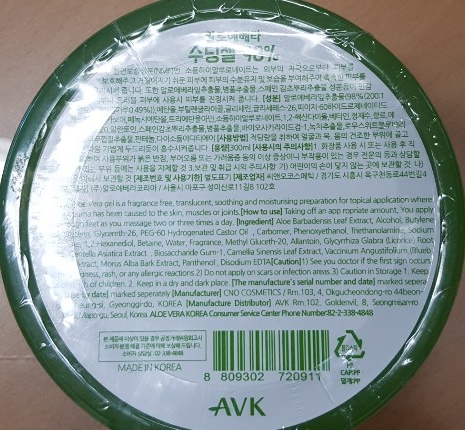 DRUG LABEL: Aloevera Soothing Gel 98%
NDC: 72988-0001 | Form: LIQUID
Manufacturer: Lydia Co., Ltd.
Category: otc | Type: HUMAN OTC DRUG LABEL
Date: 20190322

ACTIVE INGREDIENTS: GLYCERIN 0.2 g/100 mL
INACTIVE INGREDIENTS: WATER; ALOE VERA LEAF

Drug Facts

ACTIVE INGREDIENT

glycerin

INACTIVE INGREDIENT

aloe barbadensis leaf extract, alcohol, butylene glycol, etc

PURPOSE

for skin protectant

keep out of reach of the children

INDICATIONS AND USAGE

take a suitable amount on the skin

WARNINGS

■ if following abnormal symptoms occurs after use , stop use and consult with a skin specialist

red specks, swelling, itching

■ don’t use on the part where there is injury, eczema, or dermatitis

Keep out of reach of children

■ if swallowed, get medical help or contact a person control center immediately

DOSAGE AND ADMINISTRATION

for external use only